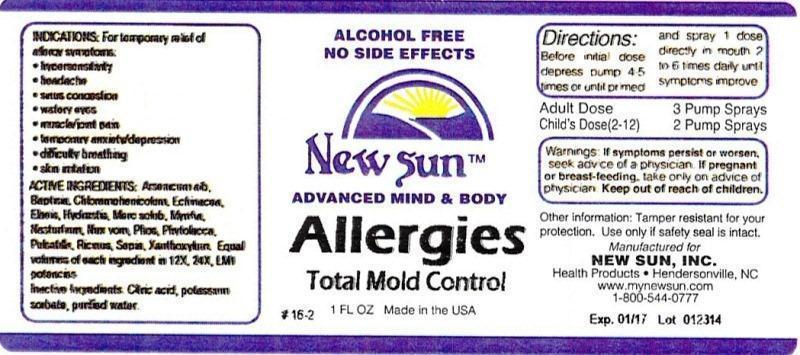 DRUG LABEL: Allergies Total Mold Control
NDC: 66579-0038 | Form: LIQUID
Manufacturer: New Sun Inc.
Category: homeopathic | Type: HUMAN OTC DRUG LABEL
Date: 20140805

ACTIVE INGREDIENTS: ARSENIC TRIOXIDE 12 [hp_X]/29 mL; BAPTISIA TINCTORIA ROOT 12 [hp_X]/29 mL; CHLORAMPHENICOL 12 [hp_X]/29 mL; ECHINACEA, UNSPECIFIED 12 [hp_X]/29 mL; ELAEIS GUINEENSIS FRUIT 12 [hp_X]/29 mL; GOLDENSEAL 12 [hp_X]/29 mL; MERCURIUS SOLUBILIS 12 [hp_X]/29 mL; MYRRH 12 [hp_X]/29 mL; NASTURTIUM OFFICINALE 12 [hp_X]/29 mL; STRYCHNOS NUX-VOMICA SEED 12 [hp_X]/29 mL; PHOSPHORUS 12 [hp_X]/29 mL; PHYTOLACCA AMERICANA ROOT 12 [hp_X]/29 mL; PULSATILLA VULGARIS 12 [hp_X]/29 mL; RICINUS COMMUNIS SEED 12 [hp_X]/29 mL; SEPIA OFFICINALIS JUICE 12 [hp_X]/29 mL; ZANTHOXYLUM AMERICANUM BARK 12 [hp_X]/29 mL
INACTIVE INGREDIENTS: CITRIC ACID MONOHYDRATE; POTASSIUM SORBATE; WATER

Allergies Total Mold Control

DOSAGE AND ADMINISTRATION

Directions: Before initial dose depress pump 4-5 times or until primed and spray 1 dose directly in mouth 2 to 6 times daily until symptoms improve.

Adult Dose: 3 Pump Sprays

Child's Dose (2-12): 2 Pump Sprays

WARNINGS

Warnings: If symptoms persist or worsen, seek advice of physician. If pregnant or breast-feeding, take only on advice of physician.

Keep out of reach of children.

Other information: Tamper resistant for your protection. Use only if safety seal is intact.

PURPOSE

Indications: For temporary relief of allergy symptoms: •hypersensitivity •headache •sinus congestion •watery eyes •muscle/joint pain •temporary anxiety/depression •difficulty breathing •skin irritation

ACTIVE INGREDIENT

Active Ingredients: Arsenicum album, Baptisia tinctoria, Chloramphenicolum, Echinacea, Elaeis guineensis, Hydrastis canadensis, Mercurius solubilis, Myrrha, Nasturtium aquaticum, Nux vomica, Phosphorus, Phytolacca decandra, Pulsatilla, Ricinus communis, Sepia, Xanthoxylum fraxineum. Equal volumes of each ingredient in 12X, 24X, LM1 potencies.

Inactive Ingredient: Citric acid, potassium sorbate, purified water.

Indications: For temporary relief of allergy symptoms:

- hypersensitivity
- headache
- sinus congestion
- watery eyes
- muscle/joint pain
- temporary anxiety/depression
- difficulty breathing
- skin irritation